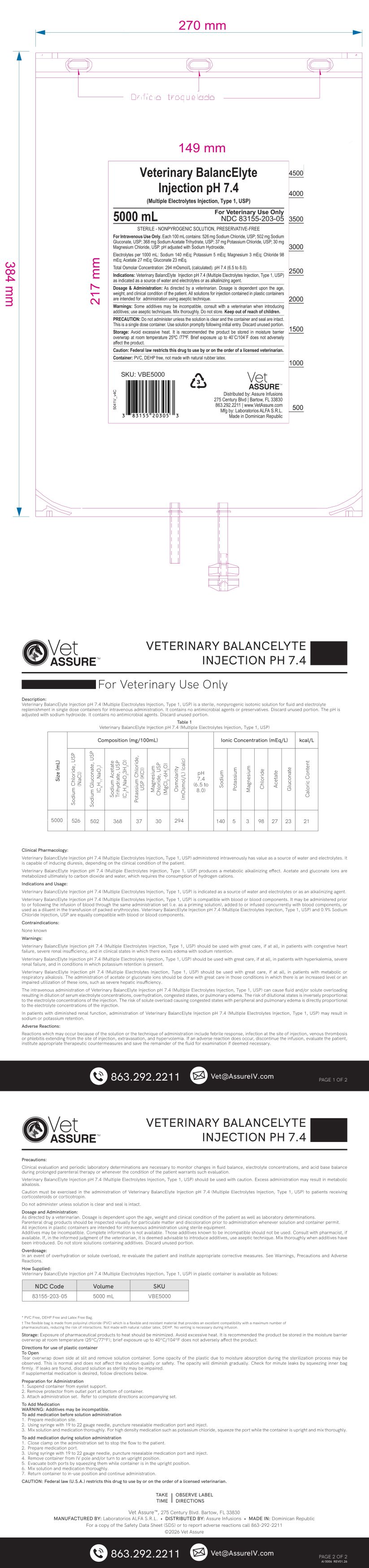 DRUG LABEL: Veterinary BalancElyte
NDC: 83155-203 | Form: INJECTION
Manufacturer: Assure Infusion, Inc
Category: animal | Type: PRESCRIPTION ANIMAL DRUG LABEL
Date: 20260222

ACTIVE INGREDIENTS: SODIUM CHLORIDE 526 mg/100 mL; SODIUM GLUCONATE 502 mg/100 mL; SODIUM ACETATE 368 mg/100 mL; POTASSIUM CHLORIDE 37 mg/100 mL; Magnesium Chloride 30 mg/100 mL
INACTIVE INGREDIENTS: WATER

Veterinary BalancElyte 5L

DOSAGE & ADMINISTRATION SECTION

As directed by a veterinarian. Dosage is dependent upon the age, weight, and clinical condition of the patient. All solutions for injection contained in plastic containers are intended for administration using aseptic technique